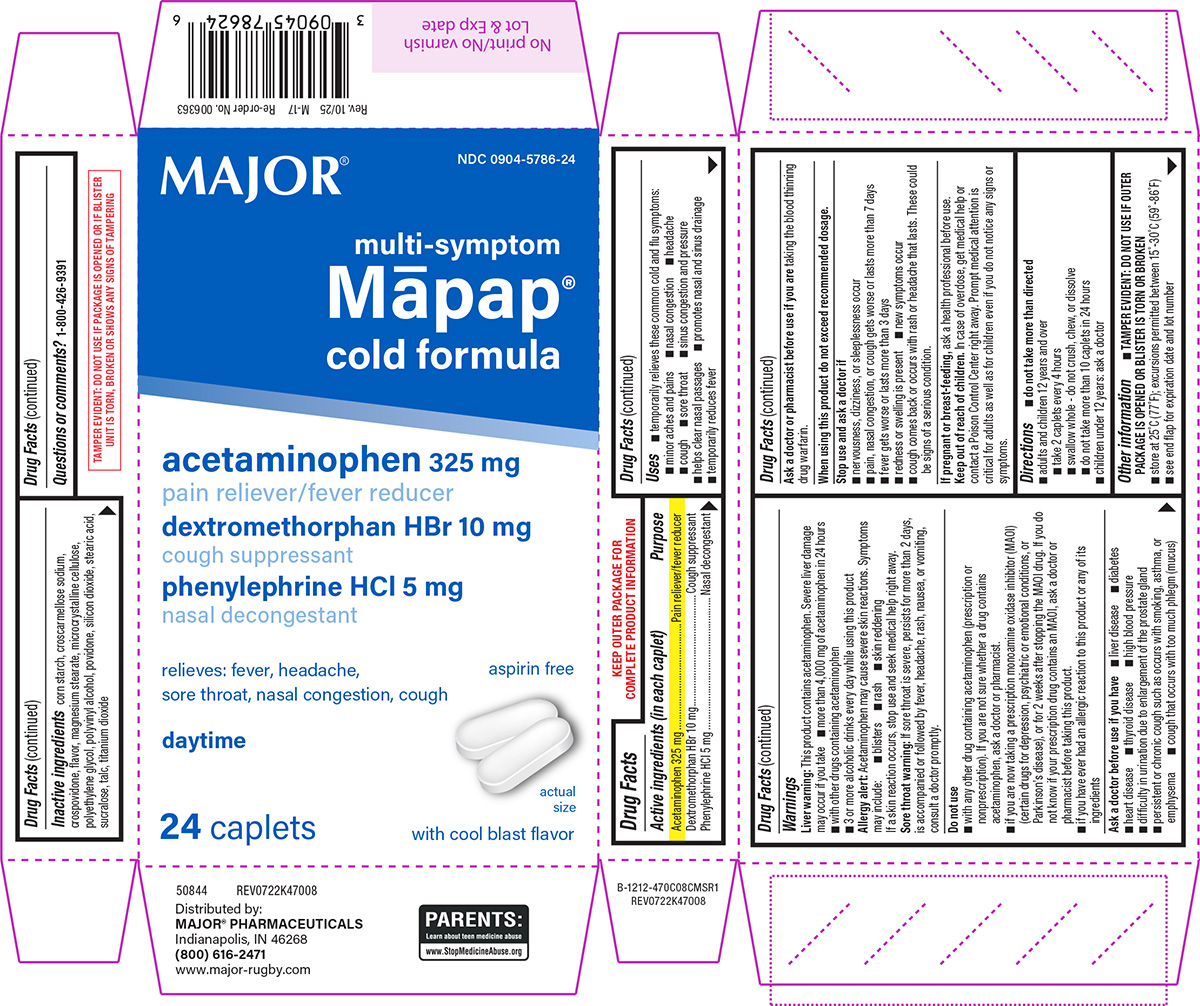 DRUG LABEL: Multi-Symptom Mapap Cold Formula
NDC: 0904-5786 | Form: TABLET, FILM COATED
Manufacturer: Major Pharmaceuticals
Category: otc | Type: HUMAN OTC DRUG LABEL
Date: 20251203

ACTIVE INGREDIENTS: ACETAMINOPHEN 325 mg/1 1; DEXTROMETHORPHAN HYDROBROMIDE 10 mg/1 1; PHENYLEPHRINE HYDROCHLORIDE 5 mg/1 1
INACTIVE INGREDIENTS: STARCH, CORN; CROSCARMELLOSE SODIUM; CROSPOVIDONE, UNSPECIFIED; MAGNESIUM STEARATE; MICROCRYSTALLINE CELLULOSE; POLYETHYLENE GLYCOL, UNSPECIFIED; POLYVINYL ALCOHOL, UNSPECIFIED; POVIDONE, UNSPECIFIED; SILICON DIOXIDE; STEARIC ACID; SUCRALOSE; TALC; TITANIUM DIOXIDE

Major 44-470C-CMS

Active ingredients (in each caplet)

Acetaminophen 325 mg
Dextromethorphan HBr 10 mg
Phenylephrine HCl 5 mg

Purpose

Pain reliever/fever reducer
Cough suppressant
Nasal decongestant

Uses

- temporarily relieves these common cold and flu symptoms:
  - minor aches and pains
  - nasal congestion
  - headache
  - cough
  - sore throat
  - sinus congestion and pressure
- helps clear nasal passages
- promotes nasal and sinus drainage
- temporarily reduces fever

Warnings

Liver warning: This product contains acetaminophen. Severe liver damage may occur if you take

- more than 4,000 mg of acetaminophen in 24 hours
- with other drugs containing acetaminophen
- 3 or more alcoholic drinks every day while using this product

Allergy alert: Acetaminophen may cause severe skin reactions. Symptoms may include:

- blisters
- rash
- skin reddening

If a skin reaction occurs, stop use and seek medical help right away.

Sore throat warning: If sore throat is severe, persists for more than 2 days, is accompanied or followed by fever, headache, rash, nausea, or vomiting, consult a doctor promptly.

Do not use

- with any other drug containing acetaminophen (prescription or nonprescription). If you are not sure whether a drug contains acetaminophen, ask a doctor or pharmacist.
- if you are now taking a prescription monoamine oxidase inhibitor (MAOI) (certain drugs for depression, psychiatric or emotional conditions, or Parkinson’s disease), or for 2 weeks after stopping the MAOI drug. If you do not know if your prescription drug contains an MAOI, ask a doctor or pharmacist before taking this product.
- if you have ever had an allergic reaction to this product or any of its ingredients

Ask a doctor before use if you have

- liver disease
- diabetes
- heart disease
- thyroid disease
- high blood pressure
- difficulty in urination due to enlargement of the prostate gland
- persistent or chronic cough such as occurs with smoking, asthma, or emphysema
- cough that occurs with too much phlegm (mucus)

Ask a doctor or pharmacist before use if you are

taking the blood thinning drug warfarin.

When using this product

do not exceed recommended dosage.

Stop use and ask a doctor if

- nervousness, dizziness, or sleeplessness occur
- pain, nasal congestion, or cough gets worse or lasts more than 7 days
- fever gets worse or lasts more than 3 days
- redness or swelling is present
- new symptoms occur
- cough comes back or occurs with rash or headache that lasts. These could be signs of a serious condition.

If pregnant or breast-feeding,

ask a health professional before use.

Keep out of reach of children.

In case of overdose, get medical help or contact a Poison Control Center right away. Prompt medical attention is critical for adults as well as for children even if you do not notice any signs or symptoms.

Directions

- do not take more than directed
- adults and children 12 years and over
  - take 2 caplets every 4 hours
  - swallow whole - do not crush, chew, or dissolve
  - do not take more than 10 caplets in 24 hours
- children under 12 years: ask a doctor

Other information

- TAMPER EVIDENT: DO NOT USE IF OUTER PACKAGE IS OPENED OR BLISTER IS TORN OR BROKEN
- store at 25°C (77°F); excursions permitted between 15°-30°C (59°-86°F)
- see end flap for expiration date and lot number

Inactive ingredients

corn starch, croscarmellose sodium, crospovidone, flavor, magnesium stearate, microcrystalline cellulose, polyethylene glycol, polyvinyl alcohol, povidone, silicon dioxide, stearic acid, sucralose, talc, titanium dioxide

Questions or comments?

1-800-426-9391

Principal Display Panel

MAJOR®

NDC 0904-5786-24

multi-symptom
Mapap®
cold formula

acetaminophen 325 mg
pain reliever/fever reducer
dextromethorphan HBr 10 mg
cough suppressant
phenylephrine HCl 5 mg
nasal decongestant

relieves: fever, headache,
sore throat, nasal congestion, cough

aspirin free

daytime

actual
size

24 CAPLETS
with cool blast flavor

TAMPER EVIDENT: DO NOT USE IF PACKAGE IS OPENED OR IF BLISTER
UNIT IS TORN, BROKEN OR SHOWS ANY SIGNS OF TAMPERING

50844 REV0722K47008

Distributed by:
MAJOR® PHARMACEUTICALS
Indianapolis, IN 46268
(800) 616-2471
www.major-rugby.com

Rev. 10/25 M-17 Re-order No. 006363

PARENTS:
Learn about teen medicine abuse
www.StopMedicineAbuse.org

Major 44-470-CMS